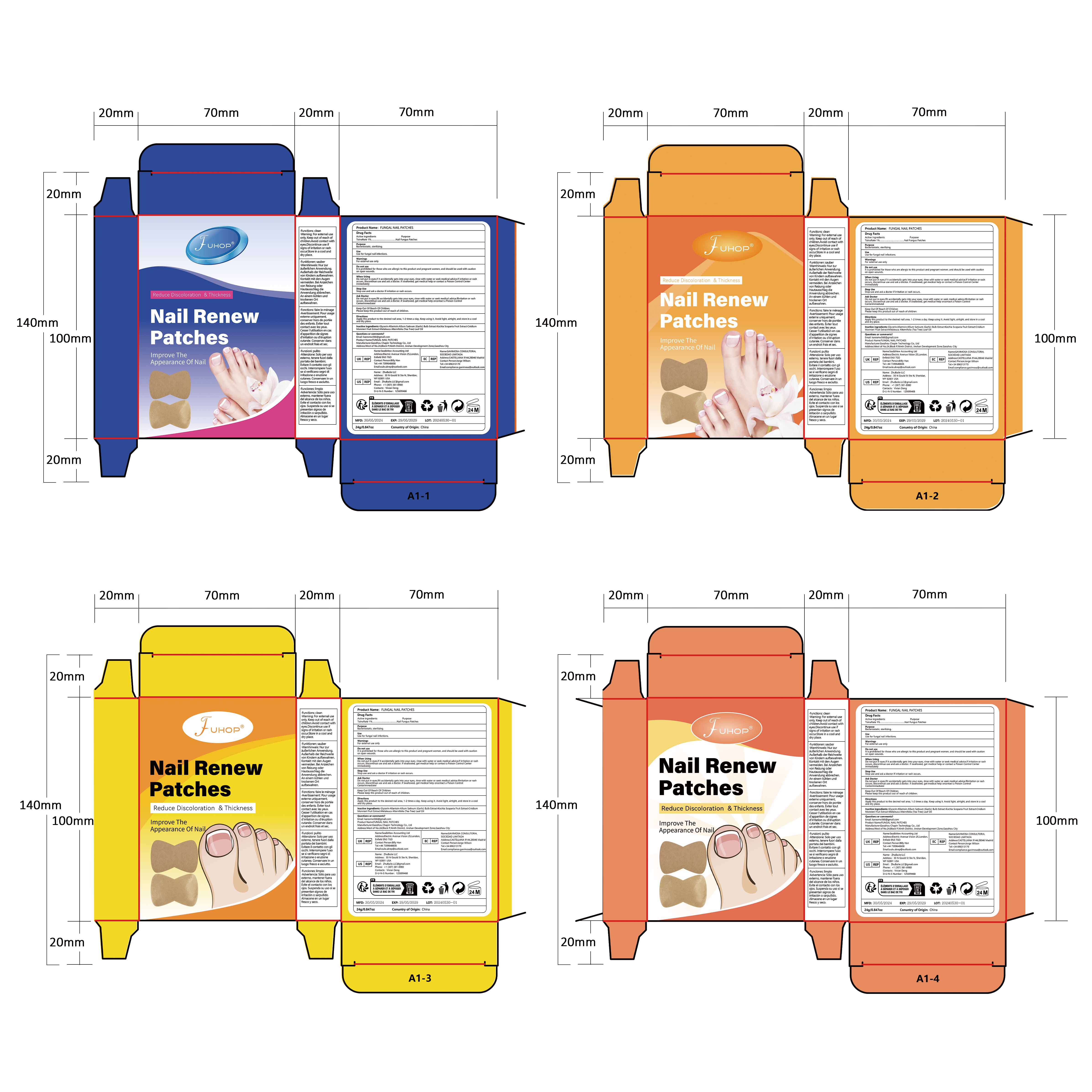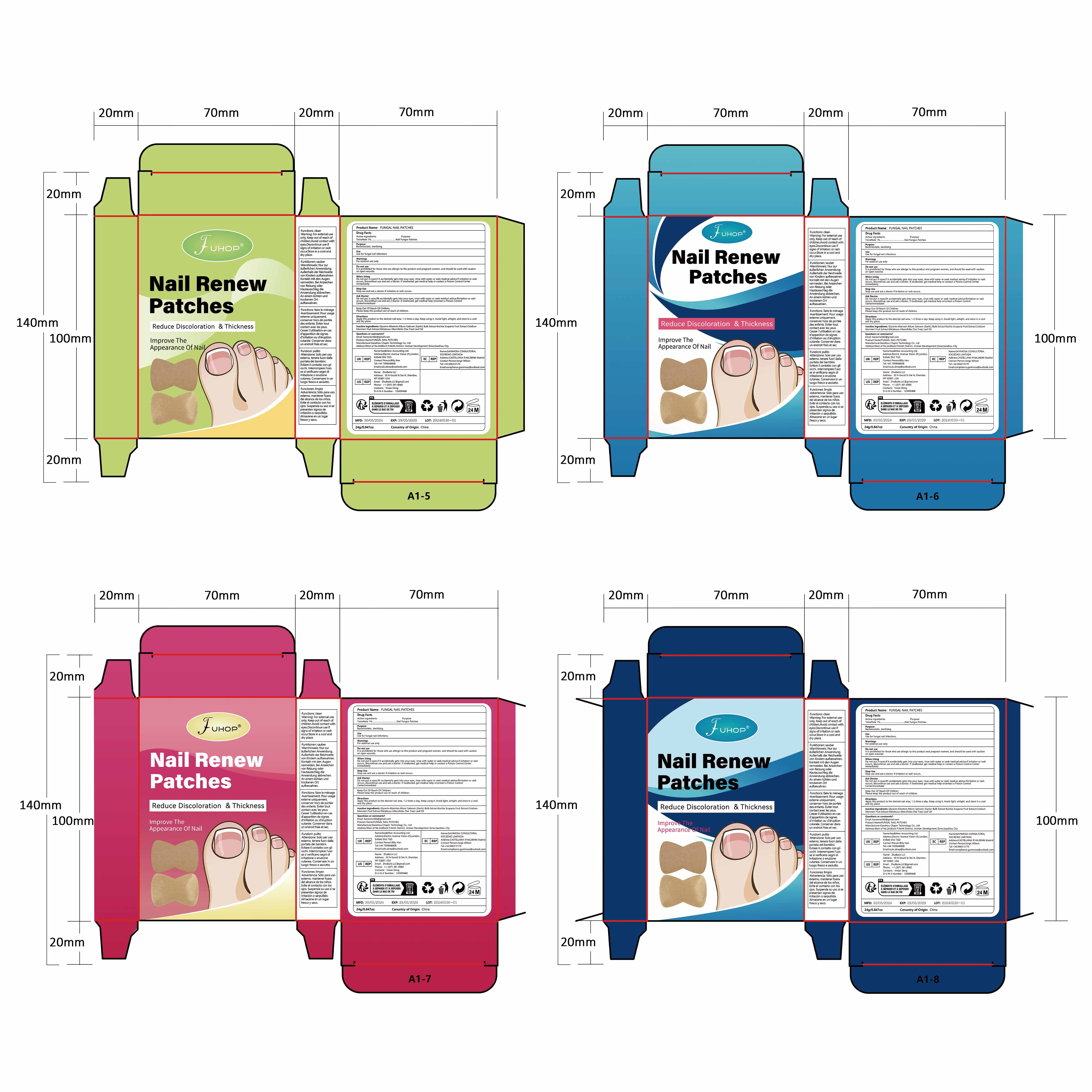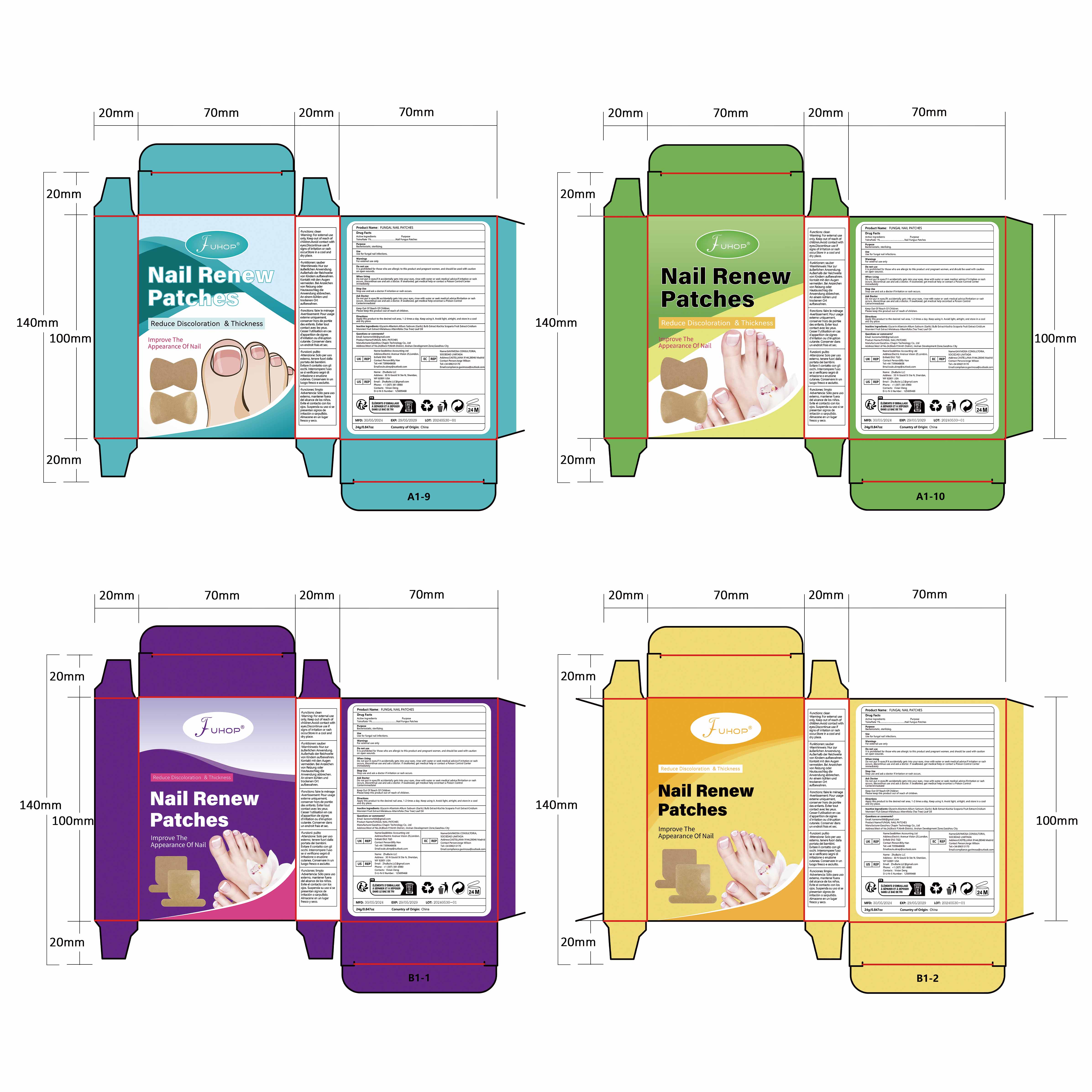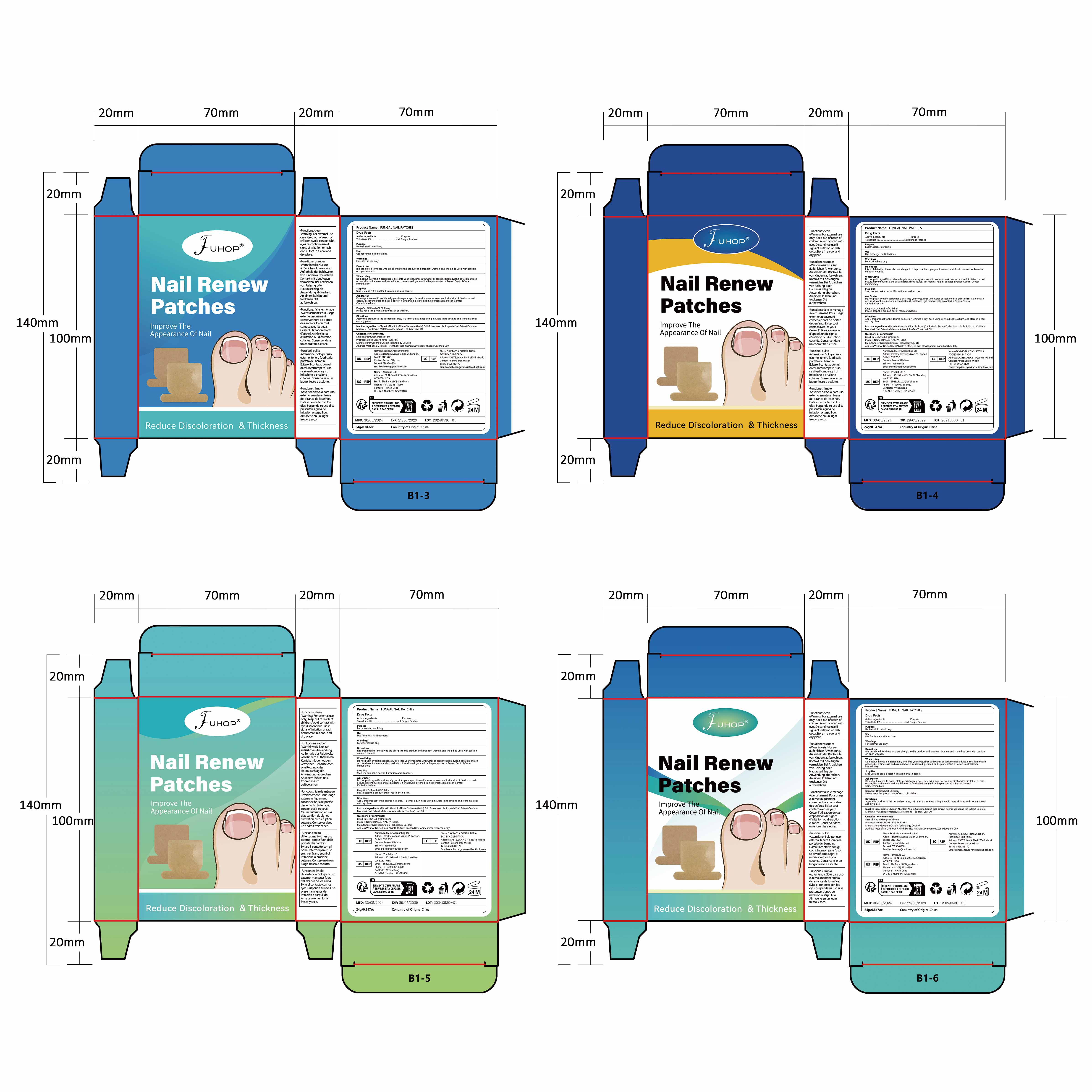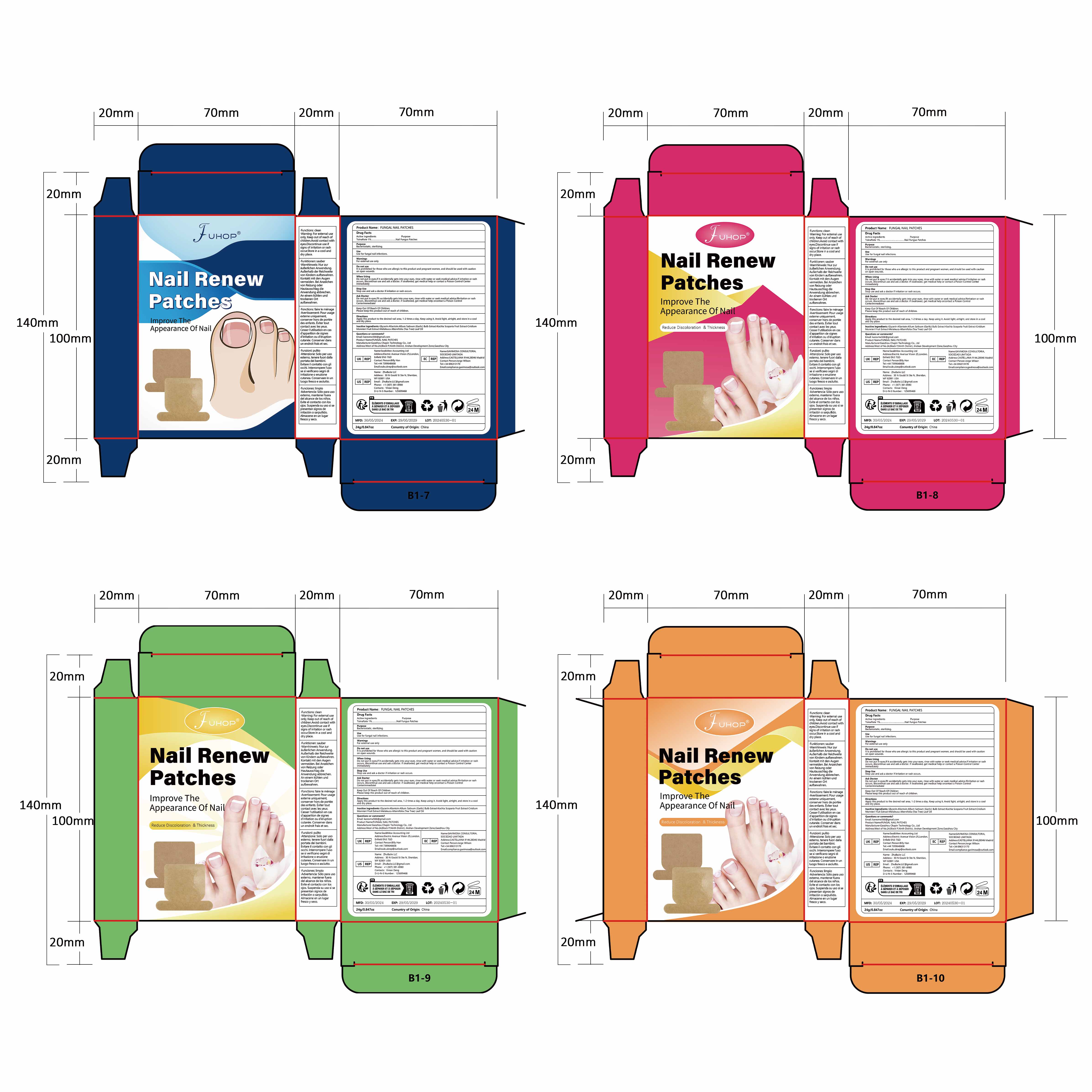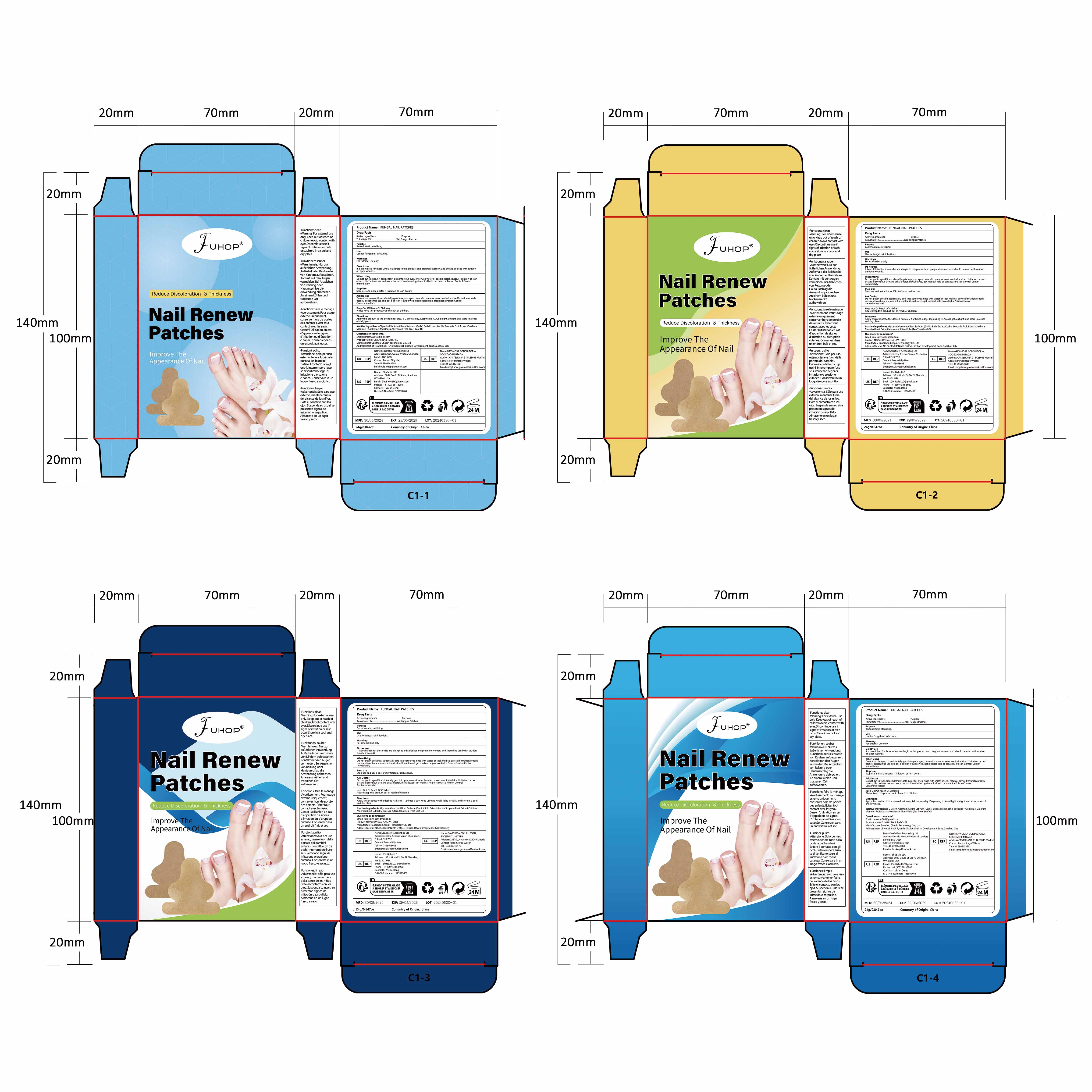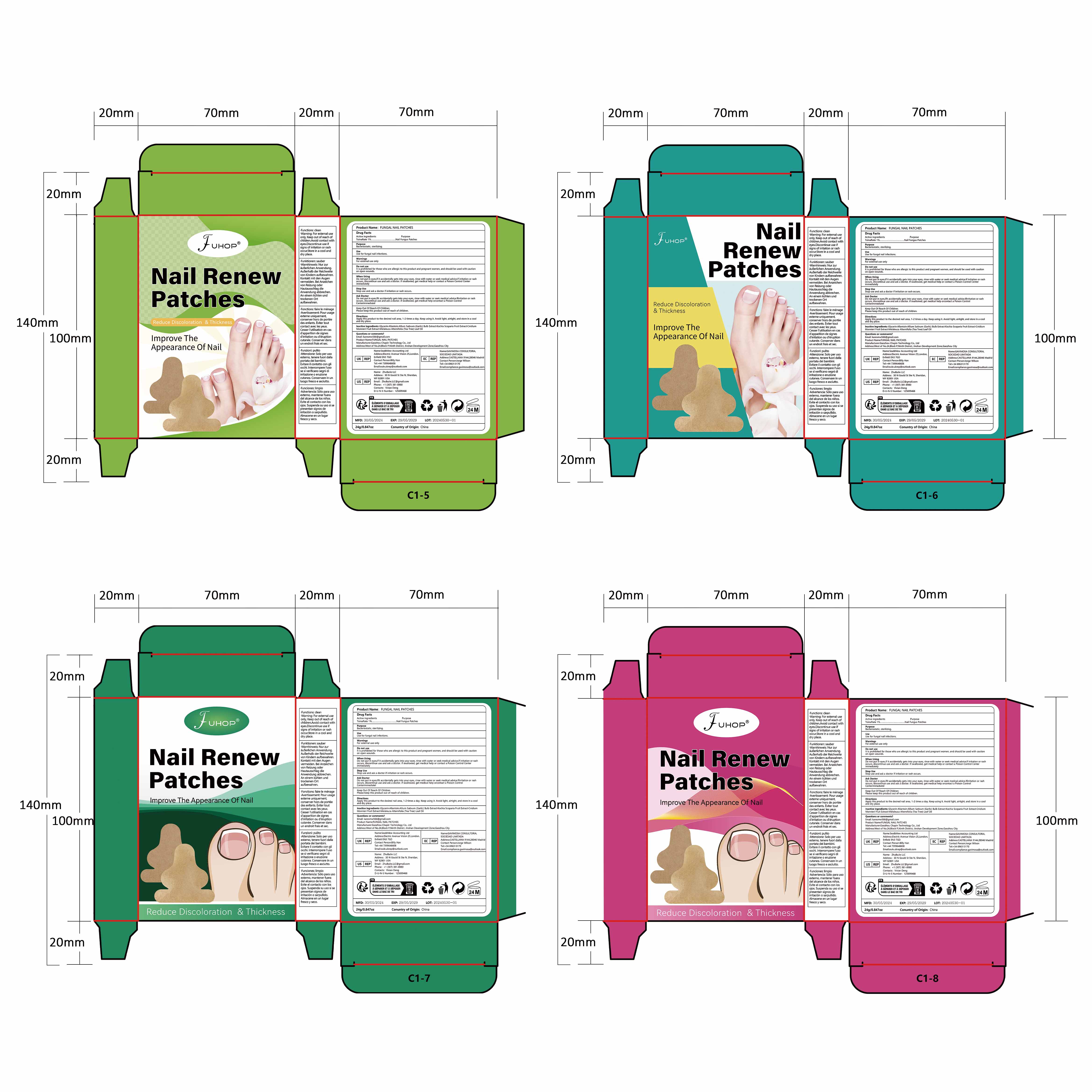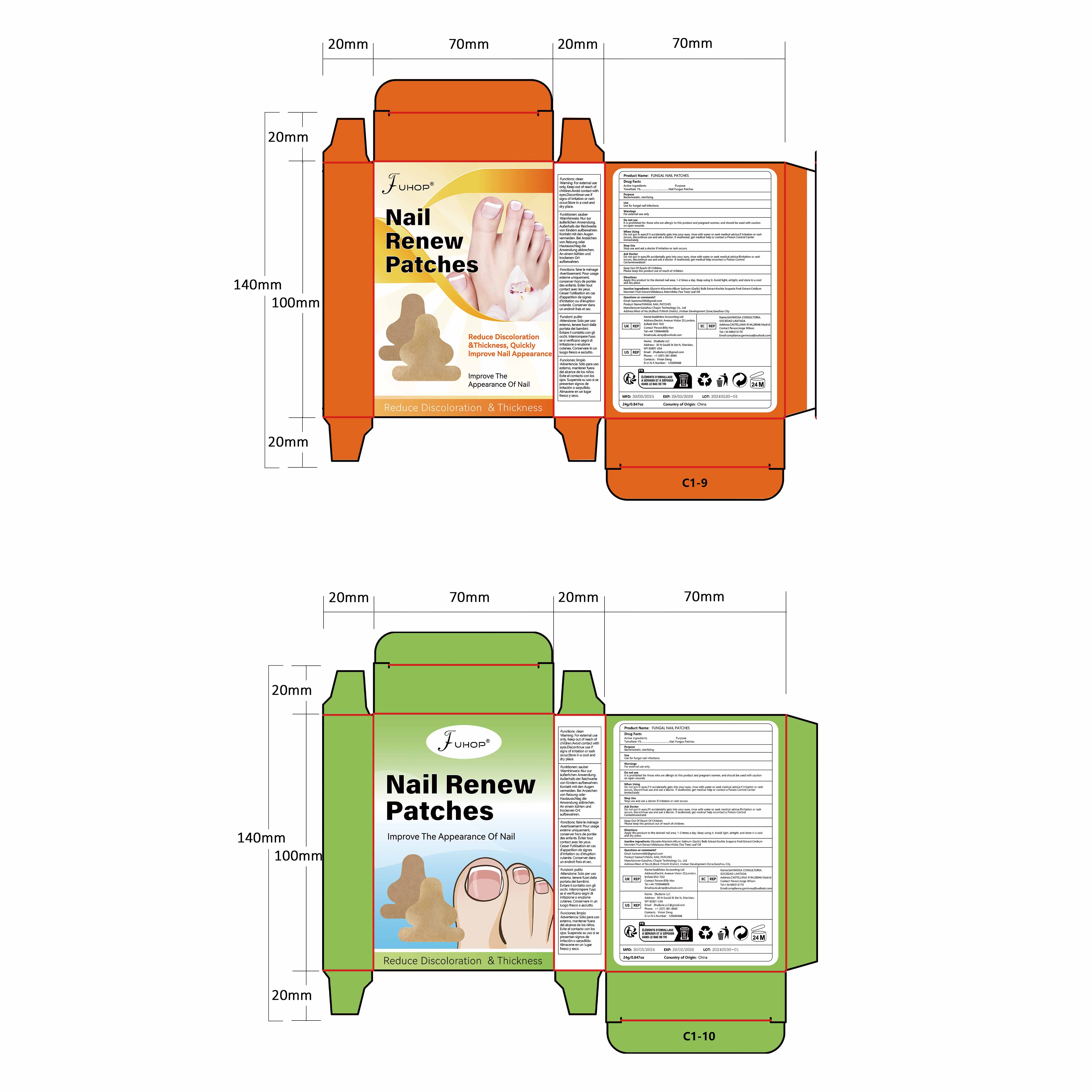 DRUG LABEL: FUHOP FUNGAL NAIL PATCHES
NDC: 84168-036 | Form: PATCH
Manufacturer: Gaozhou Chapin Technology Co., Ltd
Category: otc | Type: HUMAN OTC DRUG LABEL
Date: 20240629

ACTIVE INGREDIENTS: TOLNAFTATE 10 mg/1 g
INACTIVE INGREDIENTS: GARLIC; MELALEUCA ALTERNIFOLIA (TEA TREE) LEAF OIL; ALLANTOIN; GLYCERIN; CNIDIUM MONNIERI FRUIT

ACTIVE INGREDIENT

TOLNAFTATE 1%

Purpose

bacteriostatic, sterilizing

Use

Use for fungal nail infections

Warnings

For external use only

Do not use

It is prohibited for those who are allergic to this product and pregnant women, and should be used with caution on open wounds.

When Using

Do not put in eyes,If it accidentally gets into your eyes, rinse with water or seek medical advice.If irritation or rash occurs, discontinue use and ask a doctor. If swallowed, get medical help or contact a Poison Control Center immediately

Stop Use

Stop use and ask a doctor if irritation or rash occurs

Ask Doctor

Do not put in eyes,lfit accidentally gets into your eyes, rinse with water or seek medical advice.lfirritation or rash occurs, discontinue use and ask a doctor. if swallowed, get medical help orcontact a Poison Control Centerimmediate.

Keep Out Of Reach Of Children

Please keep this product out of reach of children

DOSAGE & ADMINISTRATION SECTION

One patch per day, each patch contains 1 mg of tolnaftate

Inactive ingredients

Glycerin, Allantoin,Allium Sativum (Garlic) Bulb Extract,Cnidium,Monnieri Fruit Oil,Melaleuca Alternifolia (Tea Tree) Leaf oil

Directions

Apply this product to the desired nail area, 1-2 times a day. Keep using it.
Avoid light, airtight, and store in a cool and dry place.